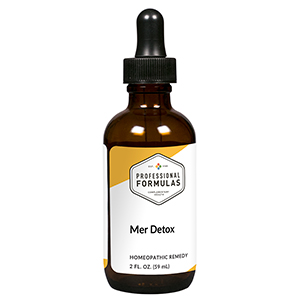 DRUG LABEL: Mer Detox
NDC: 63083-6019 | Form: LIQUID
Manufacturer: Professional Complementary Health Formulas
Category: homeopathic | Type: HUMAN OTC DRUG LABEL
Date: 20190815

ACTIVE INGREDIENTS: BAPTISIA TINCTORIA WHOLE 3 [hp_X]/59 mL; GOLDENSEAL 5 [hp_X]/59 mL; POTASSIUM DICHROMATE 6 [hp_X]/59 mL; NITRIC ACID 6 [hp_X]/59 mL; CALCIUM SULFIDE 8 [hp_X]/59 mL
INACTIVE INGREDIENTS: ALCOHOL; WATER

X19

ACTIVE INGREDIENTS

Baptisia tinctoria 3X
Hydrastis canadensis 5X
Kali bichromicum 6X
Nitricum acidum 6X
Hepar sulphuris calcareum 8X

QUESTIONS

Professional Formulas

PO Box 2034 Lake Oswego, OR 97035

INDICATIONS

For the temporary relief of exhaustion or weakness, muscle soreness, minor joint pain or stiffness, headache, dizziness, dry, itchy, or cracked skin, constipation, or diarrhea due to sensitivity to or exposure to amalgam fillings or related compounds.*

PURPOSE

*Claims based on traditional homeopathic practice, not accepted medical evidence. Not FDA evaluated.

WARNINGS

Consult a doctor if condition worsens or symptoms persist. Keep out of the reach of children. In case of overdose, get medical help or contact a poison control center right away. If pregnant or breastfeeding, ask a healthcare professional before use.

Keep out of the reach of children.

PREGNANCY OR BREAST FEEDING

If pregnant or breastfeeding, ask a healthcare professional before use.

DIRECTIONS

Place drops under tongue 30 minutes before/after meals. Adults and children 12 years and over: Take 10 drops up to 3 times per day. Consult a physician for use in children under 12 years of age.

OTHER INFORMATION

Tamper resistant. If seal is broken, do not use. After opening, close container tightly and store at room temperature away from heat.

INACTIVE INGREDIENTS

20% ethanol, purified water.

LABEL

Est 1985

Professional Formulas

Complementary Health

Mer Detox

Homeopathic Remedy

2 FL. OZ. (59 mL)